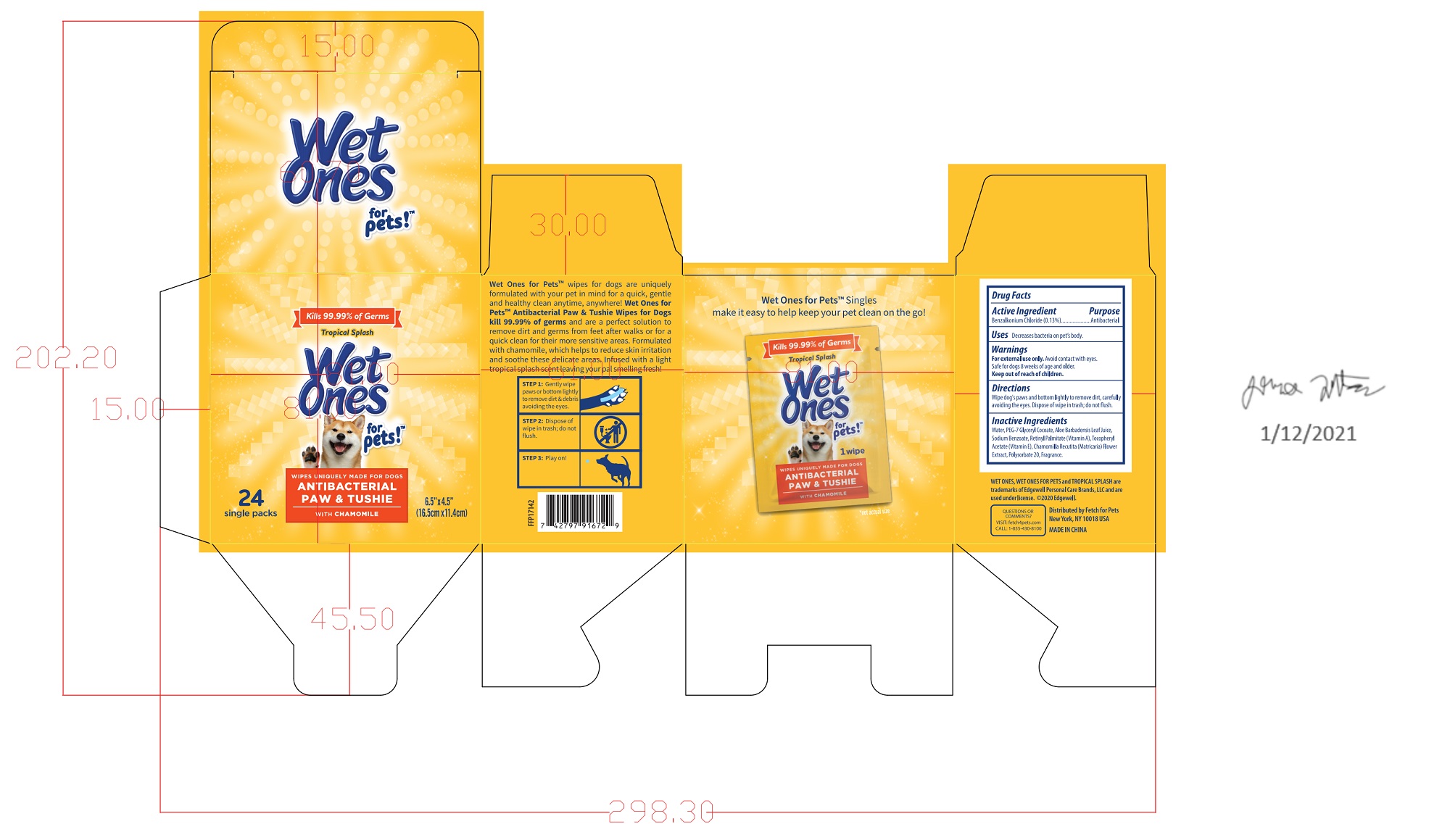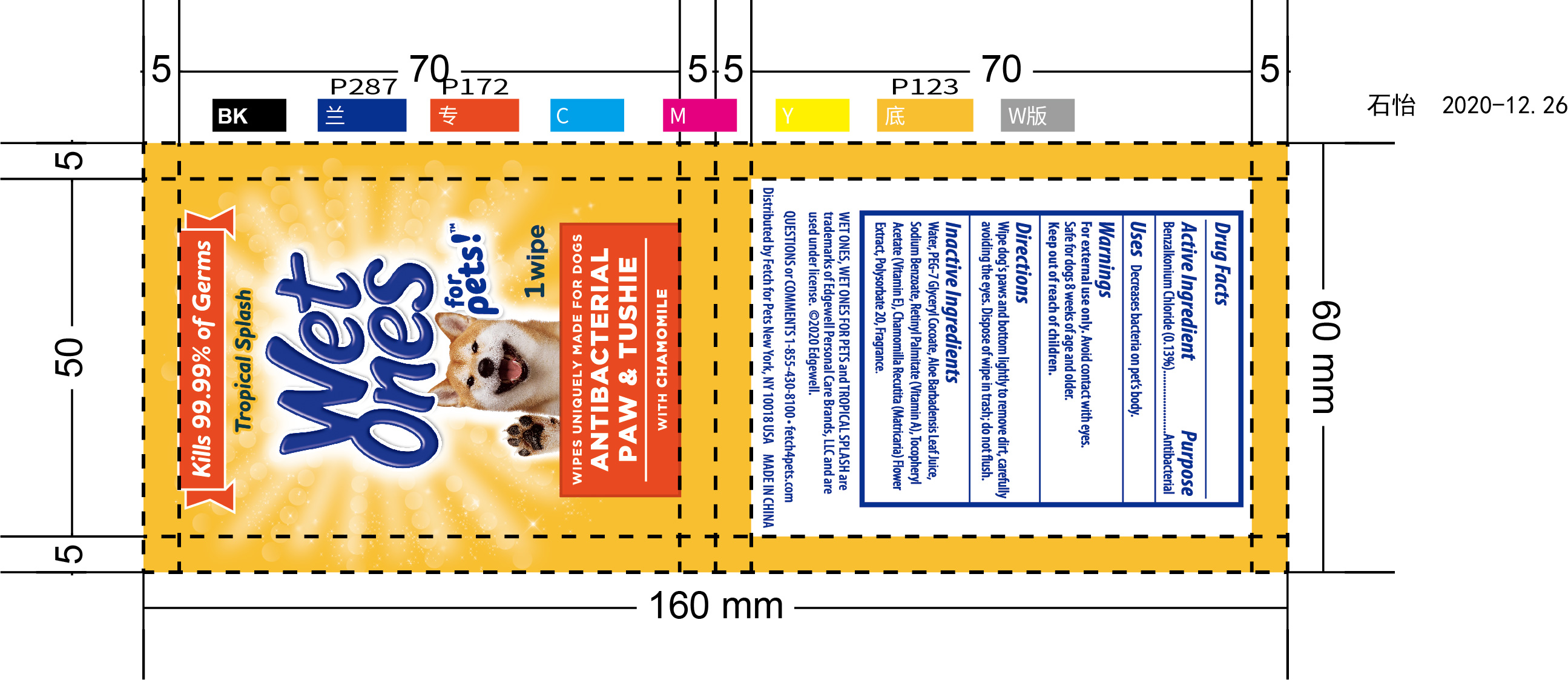 DRUG LABEL: Antibacterial Paw Tushie wipes
NDC: 77720-020 | Form: CLOTH
Manufacturer: Skaffles Group Limited Liability Company
Category: animal | Type: OTC ANIMAL DRUG LABEL
Date: 20210119

ACTIVE INGREDIENTS: BENZALKONIUM CHLORIDE 0.13 g/100 g
INACTIVE INGREDIENTS: WATER; VITAMIN A PALMITATE; .ALPHA.-TOCOPHEROL ACETATE; ALOE VERA LEAF; POLYSORBATE 20; CHAMOMILE; SODIUM BENZOATE; PEG-7 GLYCERYL COCOATE

Active Ingredient

Benzalkonium Chloride 0.13%

Purpose

Antibacterial

USE

Decreases Bacteria on pet]s body.

Warning

For external use only.

Avoid Contact with eyes. Safe for dogs 8 weeks of age and older.

Keep out of reach of children.

Directions

Wipe dog's paws and bottom lightly to remove dirt, carefully avoiding the eyes.

didpose of wipe in trash ,do not flush

Inactive ingredients

Water, PEG-7 Glyeryl Cocoate, Aloe Barbadensis Leaf Juice, Sodium Benzoate, Retinyl Palmitate (Vitamin A), Tocophery Acetate (Vitamin E), Chamomilla Recutita (Matricaria) Flower Extract, Polysorbate 20, Fragrance